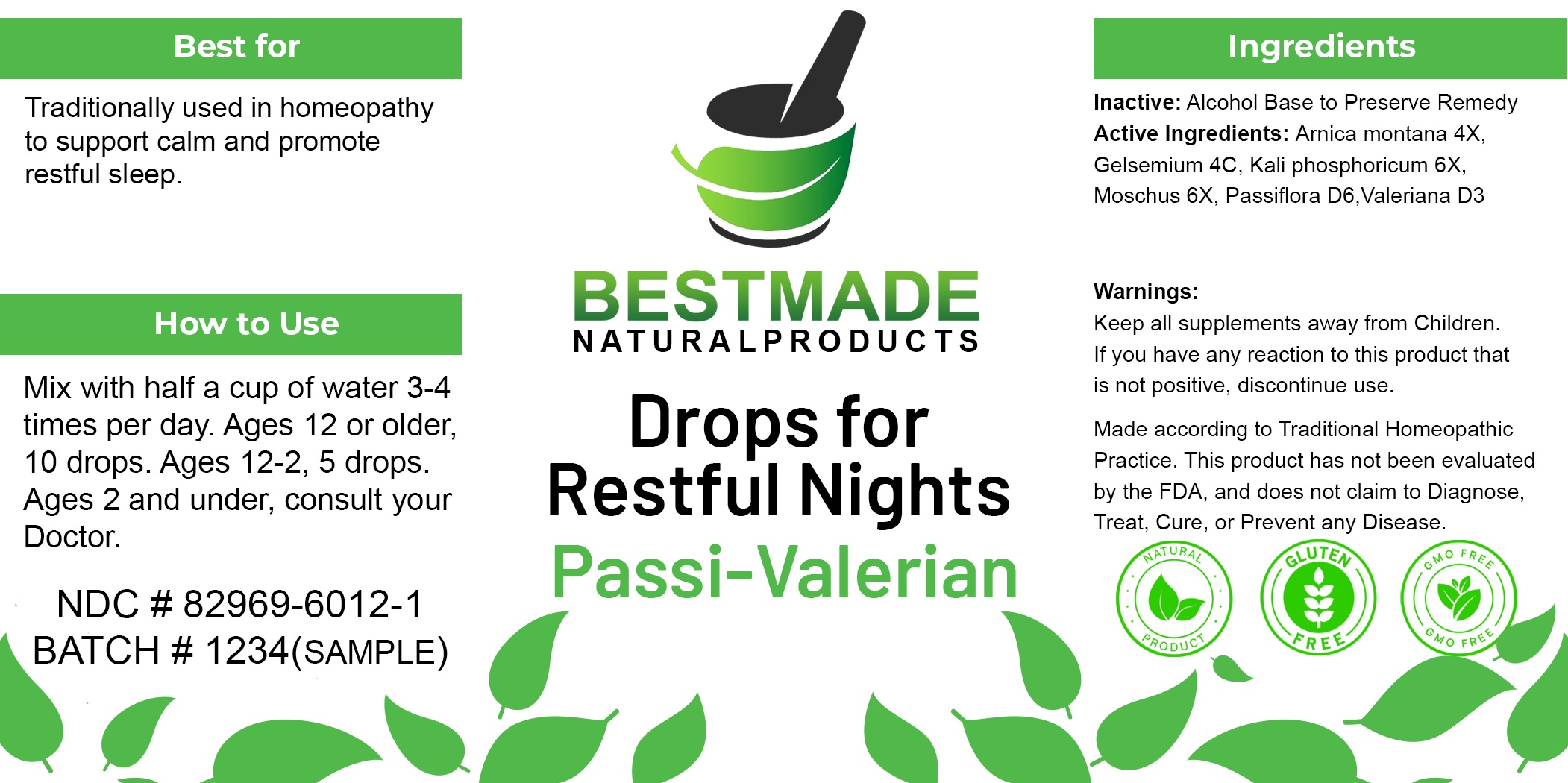 DRUG LABEL: Bestmade Natural Products Passi-Valerian
NDC: 82969-6012 | Form: LIQUID
Manufacturer: Bestmade Natural Products
Category: homeopathic | Type: HUMAN OTC DRUG LABEL
Date: 20241220

ACTIVE INGREDIENTS: PASSIFLORA INCARNATA FLOWERING TOP 30 [hp_C]/30 [hp_C]; GELSEMIUM SEMPERVIRENS ROOT 30 [hp_C]/30 [hp_C]; VALERIAN 30 [hp_C]/30 [hp_C]; POTASSIUM PHOSPHATE 30 [hp_C]/30 [hp_C]; ARNICA MONTANA 30 [hp_C]/30 [hp_C]; MOSCHUS MOSCHIFERUS MUSK SAC RESIN 30 [hp_C]/30 [hp_C]
INACTIVE INGREDIENTS: ALCOHOL 30 [hp_C]/30 [hp_C]

Homeopathic Drops for Restful Nights - Passi-Valerian, 30mL

DOSAGE AND ADMINISTRATION

Mix with half a cup of water one hour before bedtime 3-4 times per day. Ages 12 or older, 25-30 drops. Ages 12-2, 10 drops. Ages 2 and under, consult your Doctor.

INDICATIONS AND USAGE

Traditionally used in homeopathy to support calm and promote restful sleep.

Inactive: Alcohol Base to Preserve Remedy

ACTIVE INGREDIENT

Arnica montana 4X: 0.20mL

Gelsemium 4C: 0.25mL

Kali phosphoricum 6X: 0.10mL

Moschus 6X: 0.10mL

Passiflora D6: 1.50mL

Valeriana D3: 1.50mL

Keep all supplements away from Children.

PURPOSE

Traditionally used in homeopathy to support calm and promote restful sleep.

WARNINGS

If you have any reaction to this product that
is not positive, discontinue use.

Entire package label.